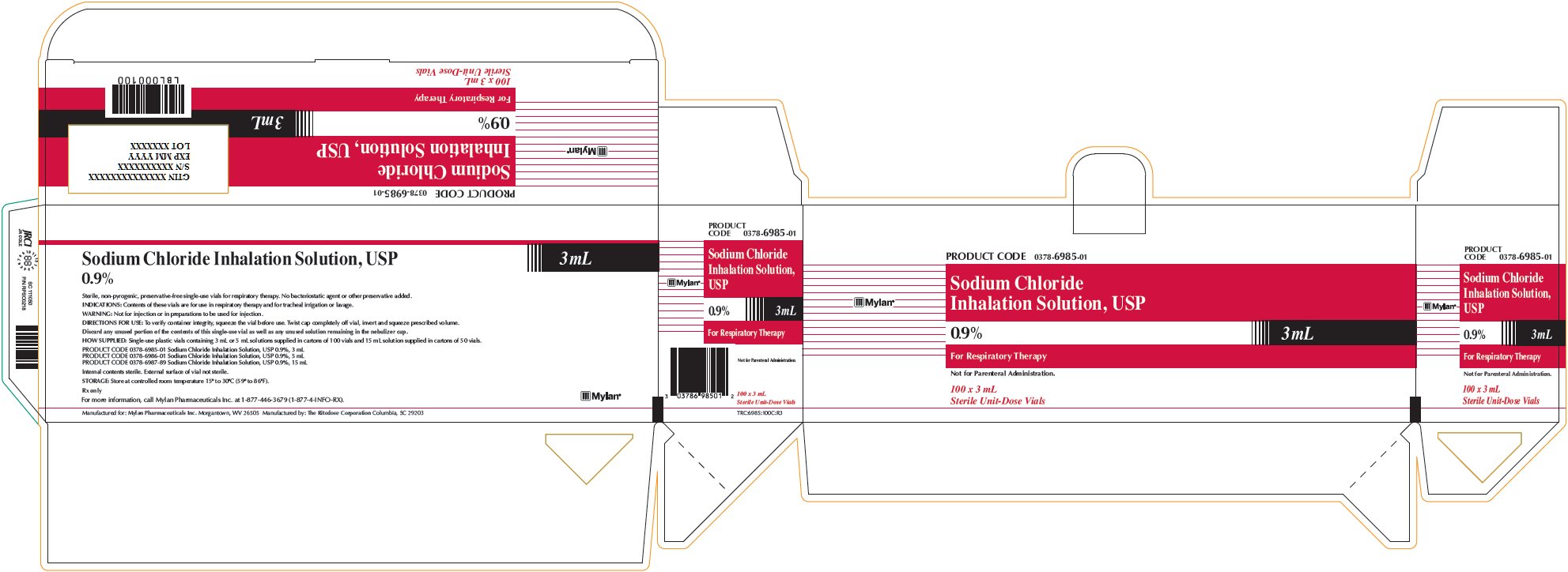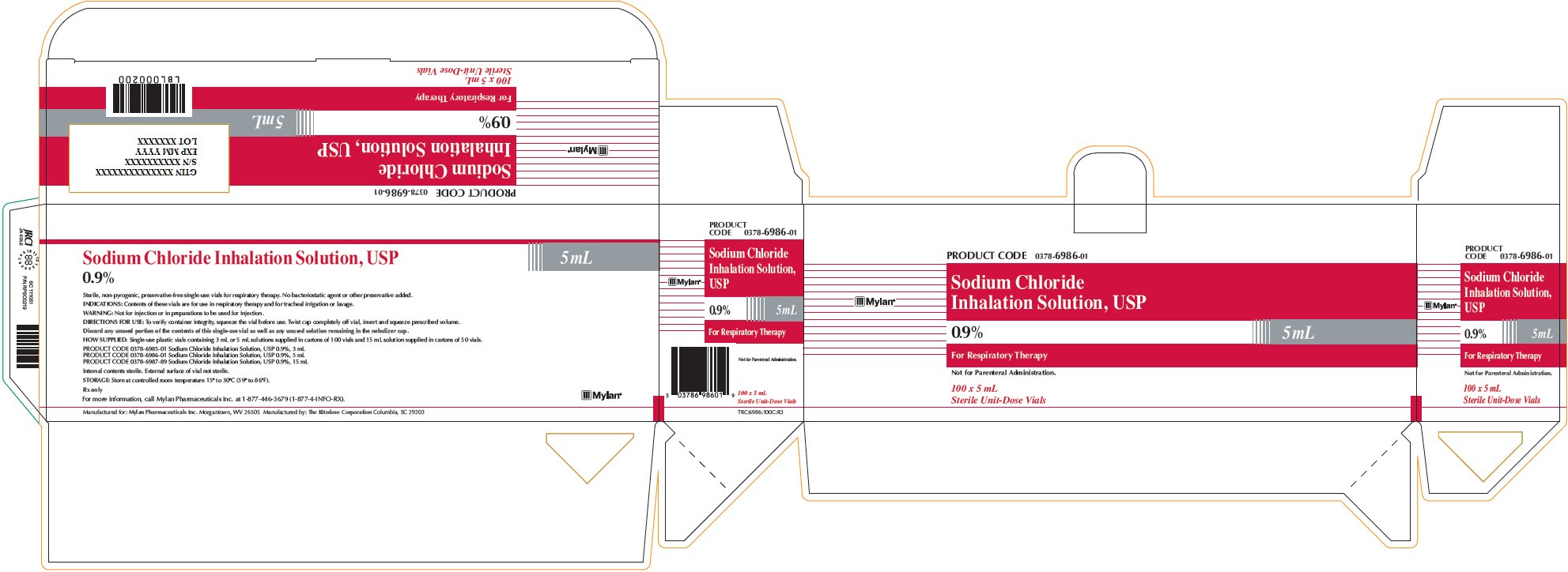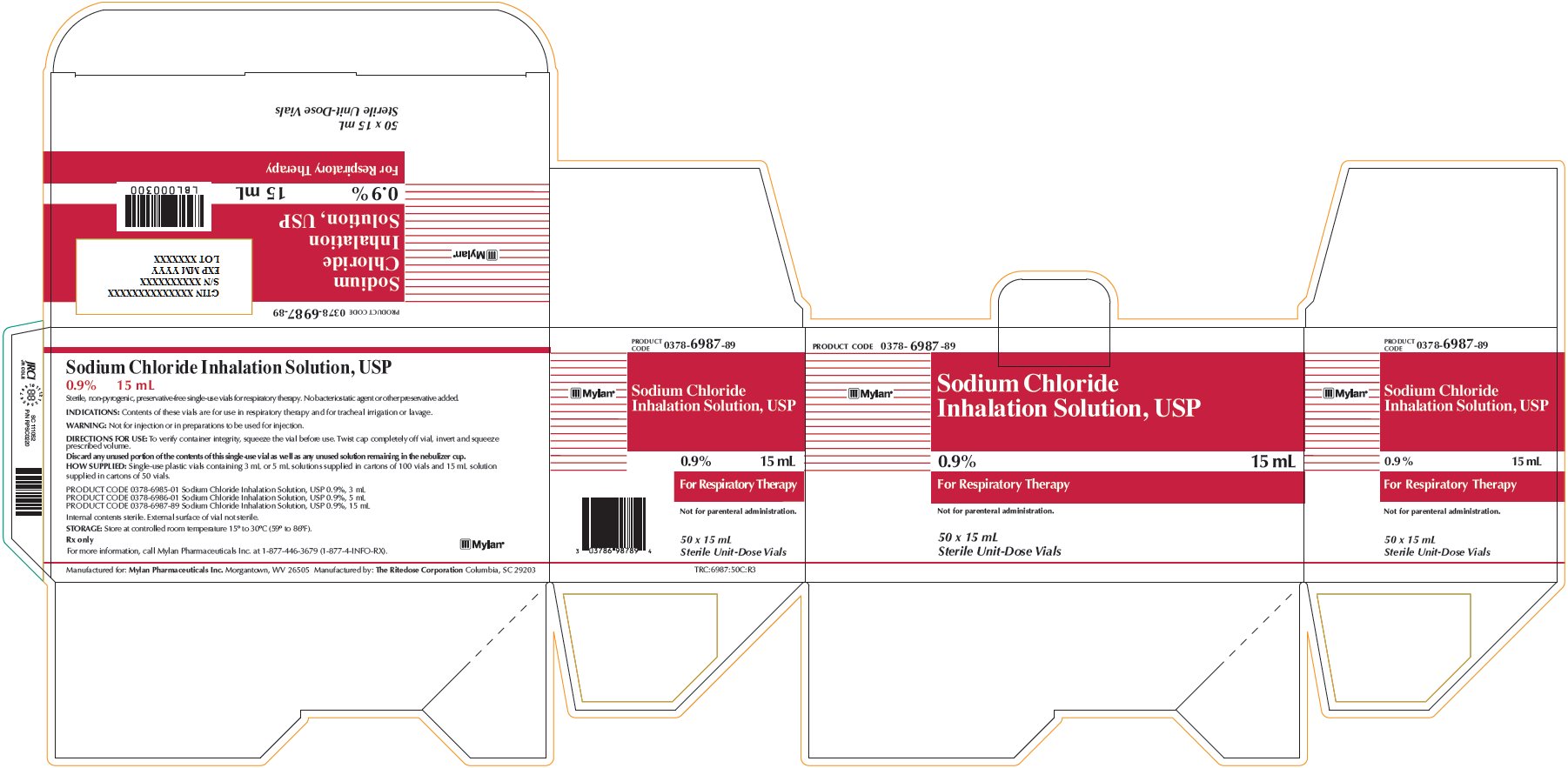 DRUG LABEL: Sodium Chloride
NDC: 0378-6985
Manufacturer: Mylan Pharmaceuticals Inc.
Category: other | Type: MEDICAL DEVICE
Date: 20161202

ACTIVE INGREDIENTS: SODIUM CHLORIDE 0.027 g/3 mL

Sodium Chloride Inhalation Solution 0.9% 3 mL

PRODUCT CODE 0378-6985-01

Sodium Chloride
Inhalation Solution, USP
0.9% 3 mL

For Respiratory Therapy

Not for Parenteral Administration.

100 x 3 mL
Sterile Unit-Dose Vials

Sodium Chloride Inhalation Solution, USP
0.9% 3 mL

Sterile, non-pyrogenic, preservative-free single-use vials for respiratory therapy. No bacteriostatic agent or other preservative added.

INDICATIONS: Contents of these vials are for use in respiratory therapy and for tracheal irrigation or lavage.

WARNING: Not for injection or in preparations to be used for injection.

DIRECTIONS FOR USE: To verify container integrity, squeeze the vial before use. Twist cap completely off vial, invert and squeeze prescribed volume.

Discard any unused portion of the contents of this single-use vial as well as any unused solution remaining in the nebulizer cup.

HOW SUPPLIED: Single-use plastic vials containing 3 mL or 5 mL solutions supplied in cartons of 100 vials and 15 mL solution supplied in cartons of 50 vials.

PRODUCT CODE 0378-6985-01 Sodium Chloride Inhalation Solution, USP 0.9%, 3 mL
PRODUCT CODE 0378-6986-01 Sodium Chloride Inhalation Solution, USP 0.9%, 5 mL
PRODUCT CODE 0378-6987-89 Sodium Chloride Inhalation Solution, USP 0.9%, 15 mL

Internal contents sterile. External surface of vial not sterile.

STORAGE: Store at controlled room temperature 15° to 30°C (59° to 86°F).

Rx only

For more information, call Mylan Pharmaceuticals Inc. at 1-877-446-3679 (1-877-4-INFO-RX).

Manufactured for: Mylan Pharmaceuticals Inc. Morgantown, WV 26505 Manufactured by: The Ritedose Corporation Columbia, SC 29203

TRC:6985:100C:R3

Sodium Chloride Inhalation Solution 0.9% 5 mL

PRODUCT CODE 0378-6986-01

Sodium Chloride
Inhalation Solution, USP
0.9% 5 mL

For Respiratory Therapy

Not for Parenteral Administration.

100 x 5 mL
Sterile Unit-Dose Vials

Sodium Chloride Inhalation Solution, USP
0.9% 5 mL

Sterile, non-pyrogenic, preservative-free single-use vials for respiratory therapy. No bacteriostatic agent or other preservative added.

INDICATIONS: Contents of these vials are for use in respiratory therapy and for tracheal irrigation or lavage.

WARNING: Not for injection or in preparations to be used for injection.

DIRECTIONS FOR USE: To verify container integrity, squeeze the vial before use. Twist cap completely off vial, invert and squeeze prescribed volume.

Discard any unused portion of the contents of this single-use vial as well as any unused solution remaining in the nebulizer cup.

HOW SUPPLIED: Single-use plastic vials containing 3 mL or 5 mL solutions supplied in cartons of 100 vials and 15 mL solution supplied in cartons of 50 vials.

PRODUCT CODE 0378-6985-01 Sodium Chloride Inhalation Solution, USP 0.9%, 3 mL
PRODUCT CODE 0378-6986-01 Sodium Chloride Inhalation Solution, USP 0.9%, 5 mL
PRODUCT CODE 0378-6987-89 Sodium Chloride Inhalation Solution, USP 0.9%, 15 mL

Internal contents sterile. External surface of vial not sterile.

STORAGE: Store at controlled room temperature 15° to 30°C (59° to 86°F).

Rx only

For more information, call Mylan Pharmaceuticals Inc. at 1-877-446-3679 (1-877-4-INFO-RX).

Manufactured for: Mylan Pharmaceuticals Inc. Morgantown, WV 26505 Manufactured by: The Ritedose Corporation Columbia, SC 29203

TRC:6986:100C:R3

Sodium Chloride Inhalation Solution 0.9% 15 mL

PRODUCT CODE 0378-6987-89

Sodium Chloride
Inhalation Solution, USP
0.9% 15 mL

For Respiratory Therapy

Not for parenteral administration.

50 x 15 mL
Sterile Unit-Dose Vials

Sodium Chloride Inhalation Solution, USP
0.9% 15 mL

Sterile, non-pyrogenic, preservative-free single-use vials for respiratory therapy. No bacteriostatic agent or other preservative added.

INDICATIONS: Contents of these vials are for use in respiratory therapy and for tracheal irrigation or lavage.

WARNING: Not for injection or in preparations to be used for injection.

DIRECTIONS FOR USE: To verify container integrity, squeeze the vial before use. Twist cap completely off vial, invert and squeeze prescribed volume.

Discard any unused portion of the contents of this single-use vial as well as any unused solution remaining in the nebulizer cup.

HOW SUPPLIED: Single-use plastic vials containing 3 mL or 5 mL solutions supplied in cartons of 100 vials and 15 mL solution supplied in cartons of 50 vials.

PRODUCT CODE 0378-6985-01 Sodium Chloride Inhalation Solution, USP 0.9%, 3 mL
PRODUCT CODE 0378-6986-01 Sodium Chloride Inhalation Solution, USP 0.9%, 5 mL
PRODUCT CODE 0378-6987-89 Sodium Chloride Inhalation Solution, USP 0.9%, 15 mL

Internal contents sterile. External surface of vial not sterile.

STORAGE: Store at controlled room temperature 15° to 30°C (59° to 86°F).

Rx only

For more information, call Mylan Pharmaceuticals Inc. at 1-877-446-3679 (1-877-4-INFO-RX).

Manufactured for: Mylan Pharmaceuticals Inc., Morgantown, WV 26505 Manufactured by: The Ritedose Corporation Columbia, SC 29203

TRC:6987:50C:R3